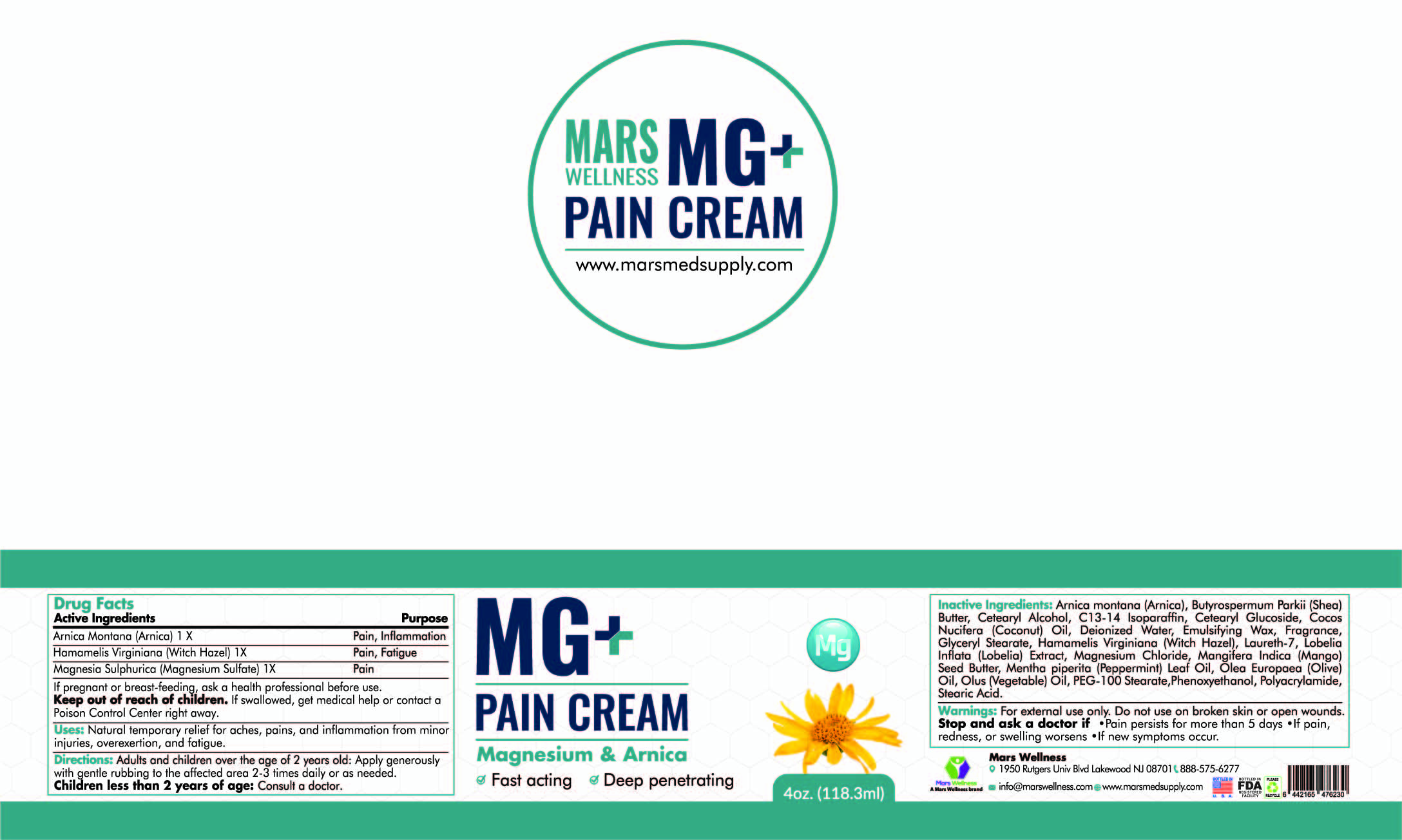 DRUG LABEL: Mars Wellness Mg PLUS Pain Cream
NDC: 76348-800 | Form: CREAM
Manufacturer: Renu Laboratories, LLC
Category: homeopathic | Type: HUMAN OTC DRUG LABEL
Date: 20250827

ACTIVE INGREDIENTS: ARNICA MONTANA 1.12 g/112 g; MAGNESIUM SULFATE ANHYDROUS 2.24 g/112 g; WITCH HAZEL 1.12 g/112 g
INACTIVE INGREDIENTS: LOBELIA INFLATA LEAF; GLYCERIN; MANGIFERA INDICA SEED BUTTER; MENTHOL; WATER; POLYETHYLENE GLYCOL 4500; CORN OIL; PEPPERMINT OIL; PHENOXYETHANOL; POLYACRYLAMIDE (10000 MW); GLYCERYL MONOSTEARATE; CETEARYL GLUCOSIDE; COCONUT OIL; WHITE WAX; SHEA BUTTER; C13-14 ISOPARAFFIN; CETOSTEARYL ALCOHOL; OLIVE OIL; STEARIC ACID; GRAPEFRUIT OIL; MAGNESIUM CHLORIDE; LAURETH-7; COMFREY LEAF; CALENDULA OFFICINALIS FLOWER; CHAMOMILE; ALOE VERA LEAF; MALVA SYLVESTRIS FLOWERING TOP; ASIAN GINSENG

Mars Wellness Mg PLUS Pain Cream

Active Ingredients

Arnica Montana 1 X

Hamamelis Virginiana 1X

Magnesia Sulphurica 1X

Warnings

For external use only. Do not use on broken skin or open wounds.

Keep out of reach of children. If swallowed get medical help or contact a Poison Control center right away.

PURPOSE

Arnica Montana Pain, Inflammation

Hamamelis Virginiana Pain, Fatigue

Magnesia Sulphurica Pain

Directions

Adults and children over the age of 2 years old: Apply generously with gentle rubbing to the affected area 2 - 3 times daily or as needed.

Children less than 2 years of age: Consult a doctor.

INACTIVE INGREDIENT

Butyrospermum Parkii (Shea) Butter, Cetearyl Alcohol, C-13-14 Isoparaffin, Cetearyl Glucoside, Cocos Nucifera (Coconut) Oil, Deionized Water, Emulsifying Wax, Fragrance, Glyceryl Stearate, Laureth-7, Lobelia Inflata (Lobelia) Extract, Mangifera Indica (Mango) Seed Butter, Mentha piperita (Peppermint) Leaf Oil, Olea europaea (Olive) Oil, Olus (Vegetable) Oil, PEG-100 Stearate, Phenoxyethanol, Polyacrylamide, Stearic Acid.

Uses

for temporary relief of minor aches and pains asssociated with

arthritis

simple backache

muscle strains

sprains

bruises

RECENT MAJOR CHANGES

SIMPLE DATE CHANGE

Nothing considered as major

QUESTIONS OR COMMENTS

MARS Wellness

1950 Rutgers Univ Blvd

Lakewood NJ 08701

888-575-6277

info@marswellness.com

www.marsmedsupply.com

Do not use on broken skin or open wounds.

Stop and ask a doctor if

- Pain persists for more than 5 days
- if pain, redness, or swelling worsens
- If new symptoms occur.

Keep out of reach of children. If swallowed, get medical help or contact a Poison Control Center right away.

PACKAGE LABEL

pPRODUCT LABELS TOP AND SIDE